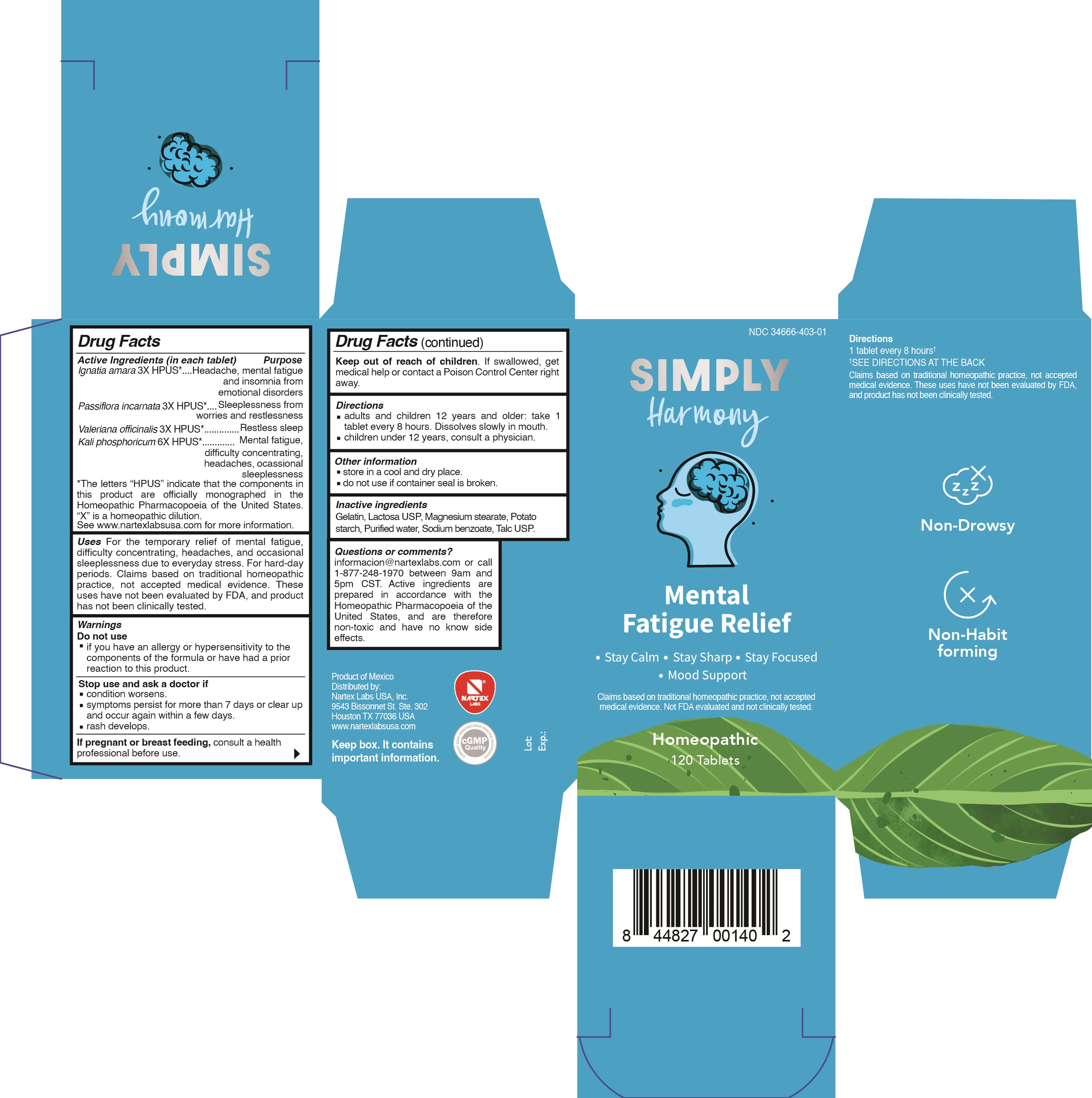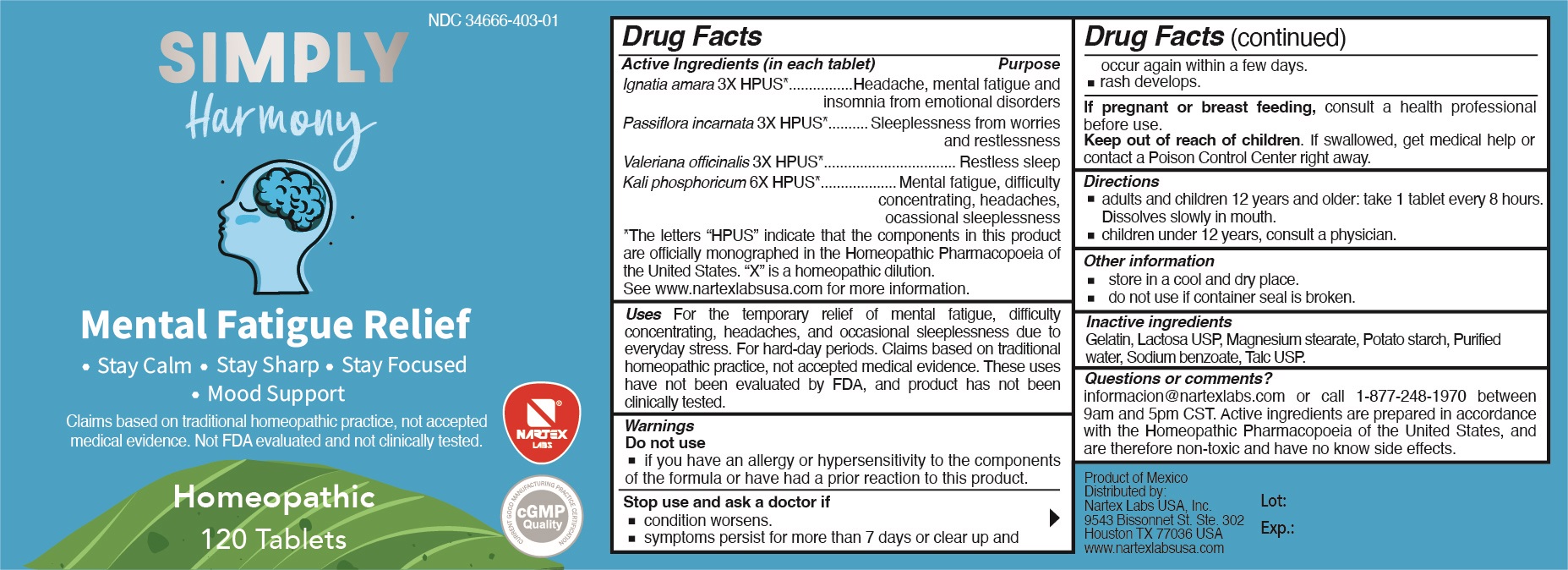 DRUG LABEL: Simply Harmony
NDC: 34666-403 | Form: TABLET
Manufacturer: Nartex Laboratorios Homeopaticos, S.A. De C.V.
Category: homeopathic | Type: HUMAN OTC DRUG LABEL
Date: 20211203

ACTIVE INGREDIENTS: PASSIFLORA INCARNATA FLOWERING TOP 3 [hp_X]/1 1; VALERIAN 3 [hp_X]/1 1; DIBASIC POTASSIUM PHOSPHATE 6 [hp_X]/1 1; STRYCHNOS IGNATII SEED 3 [hp_X]/1 1
INACTIVE INGREDIENTS: LACTOSE, UNSPECIFIED FORM; STARCH, POTATO; TALC; WATER; SODIUM BENZOATE; GELATIN; MAGNESIUM STEARATE

Simply Harmony

Active ingredients

Ignatia amara 3X HPUS*

Passiflora incarnata 3X HPUS*

Valeriana officinalis 3X HPUS*

Kali phosphoricum 6X HPUS*

Purpose

Ignatia amara 3X HPUS*.................................Headache, mental fatigue and insomnia from emotional disorders

Passiflora incarnata 3X HPUS*........................Sleeplessness from worries and restlessness

Valeriana officinalis 3X HPUS*........................Restless sleep

Kali phosphoricum 6X HPUS*.........................Mental fatigue, difficulty concentrating, headaches, occasional sleeplessness

*The letters "HPUS" indicate that the compoennts in this product are officially monographed in the Homeopathic Pharmacopoeia of the United States. "X" is a homeopathic dilution. See www.nartexlabsusa.com for more information.

Uses

For the temporary relief of mental fatigue, difficulty concentrating, headaches, and occasional sleeplessness due to everyday stress. For hard-day periods. Claims based on traditional homeopathic practice, not accepted medical evidence. These uses have not been evaluated by FDA, and product has not been clinically tested.

Warnings

Do not use

- if you have an allergy or hypersensitivity to the components of the formula or have had a prior reaction to this product.

Stop use and ask a doctor if

- conditoin worsens.
- symptoms persist for more than 7 days or clear up and occur again within a few days.
- rash develops.

PREGNANCY OR BREAST FEEDING

If pregnant or breast feeding, consult a health professional before use.

Keep out of reach of children. If swallowed, get medical help or contact a Poison Control Center right away.

Directions

- adults and children 12 years and older: take 1 tablet every 8 hours. Dissolves slowly in mouth.
- children under 12 years, consult a physician.

Other information

- store in a cool and dry place.
- do not use if container seal is broken.

Inactive ingredients

Gelatin, Lactosa USP, Magnesium stearate, Potato starch, Purified water, Sodium benzoate, Talc USP

Questions or comments?

informacion@nartexlabs.com or call 1-877-248-1970 between 9am and 5pm CST. Active ingredients are prepared in accordance with the Homeopathic Pharmacopoeia of the United States, and are therefore non-toxic and have no known side effects.

PACKAGE LABEL

NDC 34666-403-01

SIMPLY Harmony

Mental Fatigue Relief

- Stay Calm
- Stay Sharp
- Stay Focused
- Mood Support

Claims based on traditional homeopathic practice, not accepted medical evidence. Not FDA evaluated and not clinically tested.

Homeopathic

120 Tablets